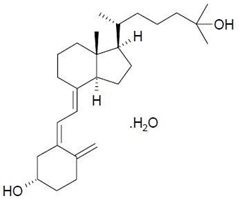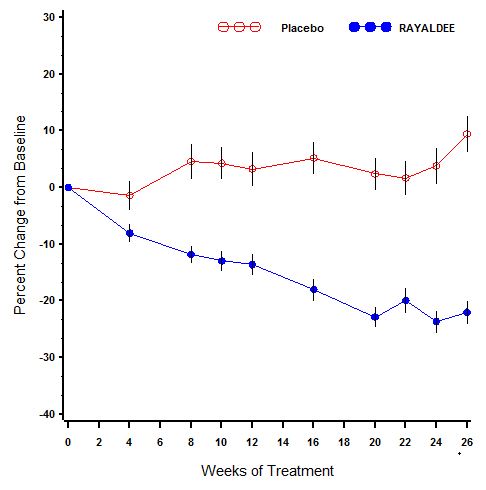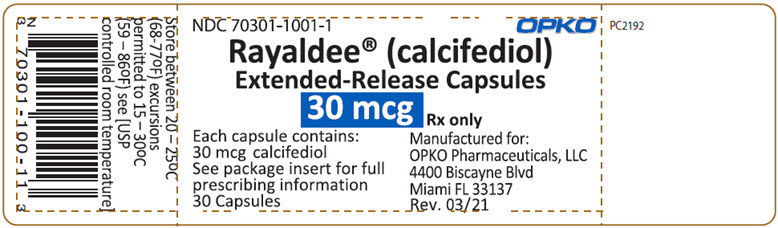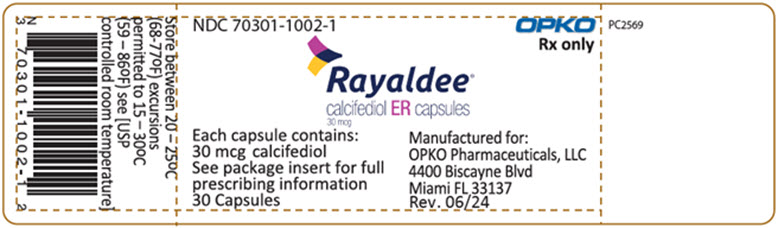 DRUG LABEL: Rayaldee
NDC: 70301-1001 | Form: CAPSULE, EXTENDED RELEASE
Manufacturer: OPKO Pharmaceuticals LLC
Category: prescription | Type: HUMAN PRESCRIPTION DRUG LABEL
Date: 20240119

ACTIVE INGREDIENTS: CALCIFEDIOL 30 ug/1 1
INACTIVE INGREDIENTS: PARAFFIN; MINERAL OIL; HYPROMELLOSE, UNSPECIFIED; GLYCERYL MONO- AND DIPALMITOSTEARATE; LAUROYL PEG-32 GLYCERIDES; ALCOHOL; BUTYLATED HYDROXYTOLUENE; MEDIUM-CHAIN TRIGLYCERIDES; HYDROXYPROPYL CORN STARCH (5% SUBSTITUTION BY WEIGHT); CARRAGEENAN; SODIUM PHOSPHATE, DIBASIC, UNSPECIFIED FORM; SORBITOL; SORBITAN; FD&C BLUE NO. 1; TITANIUM DIOXIDE; WATER

HIGHLIGHTS OF PRESCRIBING INFORMATION

These highlights do not include all the information needed to use RAYALDEE® safely and effectively. See full prescribing information for RAYALDEE.
RAYALDEE® (calcifediol) extended-release capsules, for oral use
Initial U.S. Approval: 2016

1 INDICATIONS AND USAGE

RAYALDEE is a vitamin D3 analog indicated for the treatment of secondary hyperparathyroidism in adults with stage 3 or 4 chronic kidney disease and serum total 25-hydroxyvitamin D levels less than 30 ng/mL. (1)

Limitations of Use:

RAYALDEE is not indicated in patients with stage 5 chronic kidney disease or end-stage renal disease on dialysis. (1)

2 DOSAGE AND ADMINISTRATION

- The initial dose of RAYALDEE is 30 mcg administered orally once daily at bedtime. Serum calcium should be below 9.8 mg/dL before initiating treatment. (2)
- Monitor serum calcium, phosphorus, 25-hydroxyvitamin D and intact parathyroid hormone (PTH) 3 months after starting therapy or changing dose. (2.2, 5.3)
- Increase the dose to 60 mcg once daily after 3 months if intact PTH is above the treatment goal. Ensure serum calcium is below 9.8 mg/dL, phosphorus is below 5.5 mg/dL and 25-hydroxyvitamin D is below 100 ng/mL before increasing the dose. (2.2)
- Suspend dosing if intact PTH is persistently abnormally low, serum calcium is consistently above the normal range or serum 25-hydroxyvitamin D is consistently above 100 ng/mL. (2.2)

3 DOSAGE FORMS AND STRENGTHS

Extended-release capsules: 30 mcg (3)

4 CONTRAINDICATIONS

None (4)

5 WARNINGS AND PRECAUTIONS

- Hypercalcemia: Excessive administration of vitamin D compounds, including RAYALDEE, can cause hypercalcemia and hypercalciuria. Severe hypercalcemia due to substantial overdosage of vitamin D and its metabolites may require emergency attention. Patients should be informed about the symptoms of elevated calcium. (5.1)
- Digitalis toxicity: Potentiated by hypercalcemia of any cause. Monitor serum calcium and signs and symptoms of digitalis toxicity more frequently when initiating or adjusting the dose of RAYALDEE. (5.2)
- Adynamic Bone Disease: Monitor for abnormally low levels of intact PTH levels when using RAYALDEE, and adjust dose if needed. (2.2, 5.3)

6 ADVERSE REACTIONS

The most common adverse reactions (≥3% and more frequent than placebo) were anemia, nasopharyngitis, increased blood creatinine, dyspnea, cough, congestive heart failure and constipation. (6.1)

To report SUSPECTED ADVERSE REACTIONS, contact OPKO Pharmaceuticals, LLC at 1-844-729-2539 or FDA at 1-800-FDA-1088 or www.fda.gov/medwatch.

7 DRUG INTERACTIONS

- Co-administration of cytochrome P450 inhibitors, such as ketoconazole, may alter serum levels of calcifediol. (7.1)
- Co-administration of thiazides may cause hypercalcemia. (7.2)
- Cholestyramine may impair the absorption of calcifediol. (7.3)
- The half-life of calcifediol is reduced by drugs stimulating microsomal hydroxylation, such as phenobarbital or other anticonvulsants. (7.4)

8 USE IN SPECIFIC POPULATIONS

- Lactation: Monitor infants exposed to RAYALDEE through breast milk for seizures, vomiting, constipation and weight loss. (8.2)

FULL PRESCRIBING INFORMATION

1 INDICATIONS AND USAGE

RAYALDEE is a vitamin D3 analog indicated for the treatment of secondary hyperparathyroidism in adult patients with stage 3 or 4 chronic kidney disease and serum total 25-hydroxyvitamin D levels less than 30 ng/mL.

Limitations of Use

RAYALDEE is not indicated for the treatment of secondary hyperparathyroidism in patients with stage 5 chronic kidney disease or in patients with end-stage renal disease on dialysis.

2 DOSAGE AND ADMINISTRATION

2.1 Important Dosage and Administration Information

- Ensure serum calcium is below 9.8 mg/dL before initiating treatment [see Warnings and Precautions (5.1)].
- Instruct patients to swallow RAYALDEE capsules whole.
- Instruct patients to skip a missed dose and to resume taking the medicine at the next regularly scheduled time. Do not administer an extra dose.

2.2 Starting Dose and Dose Titration

- The initial dose of RAYALDEE is 30 mcg administered orally once daily at bedtime.
- The maintenance dose of RAYALDEE should target serum total 25-hydroxyvitamin D levels between 30 and 100 ng/mL, intact parathyroid hormone (PTH) levels within the desired therapeutic range, serum calcium (corrected for low albumin) within the normal range and serum phosphorus below 5.5 mg/dL.
- Monitor serum calcium, serum phosphorus, serum total 25-hydroxyvitamin D and intact PTH levels at a minimum of 3 months after initiation of therapy or dose adjustment, and subsequently at least every 6 to 12 months.
- Increase the dose to 60 mcg orally once daily at bedtime after approximately 3 months, if intact PTH remains above the desired therapeutic range. Prior to raising the dose, ensure serum calcium is below 9.8 mg/dL, serum phosphorus is below 5.5 mg/dL and serum total 25-hydroxyvitamin D is below 100 ng/mL.
- Suspend dosing if intact PTH is persistently and abnormally low to reduce the risk of adynamic bone disease [see Warnings and Precautions (5.3)], if serum calcium is consistently above the normal range to reduce the risk of hypercalcemia [see Warnings and Precautions (5.1)], or if serum total 25-hydroxyvitamin D is consistently above 100 ng/mL. Restart at a reduced dose after these laboratory values have normalized.

3 DOSAGE FORMS AND STRENGTHS

Extended-release capsules, 30 mcg available as:

- blue oval soft capsules imprinted with “O” in white ink
- White two-piece banded hard capsules imprinted with ”O” and “30” in blue ink

4 CONTRAINDICATIONS

None.

5 WARNINGS AND PRECAUTIONS

5.1 Hypercalcemia

Hypercalcemia may occur during RAYALDEE treatment [see Adverse Reactions (6.1)]. Acute hypercalcemia may increase the risk of cardiac arrhythmias and seizures and may potentiate the effect of digitalis on the heart [see Warnings and Precautions (5.2)]. Chronic hypercalcemia can lead to generalized vascular calcification and other soft-tissue calcification. Severe hypercalcemia may require emergency attention.

Hypercalcemia may be exacerbated by concomitant administration of high doses of calcium containing preparations, thiazide diuretics, or other vitamin D compounds. In addition, high intake of calcium and phosphate concomitantly with vitamin D compounds may lead to hypercalciuria and hyperphosphatemia. In these circumstances, frequent serum calcium monitoring and RAYALDEE dose adjustments may be required. Patients with a history of hypercalcemia prior to initiating therapy with RAYALDEE should be monitored more frequently for possible hypercalcemia during therapy.

Patients should be informed about the symptoms of elevated serum calcium, which include feeling tired, difficulty thinking clearly, loss of appetite, nausea, vomiting, constipation, increased thirst, increased urination, and weight loss.

5.2 Digitalis Toxicity

Hypercalcemia of any cause, including RAYALDEE [see Warnings and Precautions (5.1)], increases the risk of digitalis toxicity. In patients using RAYALDEE concomitantly with digitalis compounds, monitor both serum calcium and patients for signs and symptoms of digitalis toxicity and increase the frequency of monitoring when initiating or adjusting the dose of RAYALDEE [see Dosage and Administration (2)].

5.3 Adynamic Bone Disease

Adynamic bone disease with subsequent increased risk of fractures may develop if intact PTH levels are suppressed by RAYALDEE to abnormally low levels. Monitor intact PTH levels and adjust RAYALDEE dose, if needed [see Dosage and Administration (2.2)].

6 ADVERSE REACTIONS

The following important adverse reactions are discussed in greater detail in other sections of the label:

- Hypercalcemia [see Warnings and Precautions (5.1)]
- Adynamic Bone Disease [see Warnings and Precautions (5.3)]

6.1 Clinical Trial Experience

Because clinical trials are conducted under widely varying conditions, adverse reaction rates observed cannot be directly compared to rates in other trials and may not reflect the rates observed in clinical practice.

The data in Table 1 are derived from two pivotal studies described below [see Clinical Studies (14)]. These data reflect exposure of 285 subjects to RAYALDEE 30 or 60 mcg daily for up to 6 months (mean 24 weeks, range 1 to 31 weeks). The mean age of the study population was 66 years old (range 25-85 years). Half of the subjects were male, 65% were White, and 32% were African-American or Black. At baseline, subjects had secondary hyperparathyroidism, stage 3 (52%) or 4 (48%) chronic kidney disease without macroalbuminuria and serum total 25-hydroxyvitamin D levels less than 30 ng/mL. The most common causes of chronic kidney disease were diabetes and hypertension and the mean estimated GFR at baseline was 31 mL/min/1.73m^2. At baseline, mean plasma intact PTH was 148 pg/mL, mean serum calcium was 9.2 mg/dL, mean serum phosphorus was 3.7 mg/dL and mean serum 25-hydroxyvitamin D was 20 ng/mL.

Table 1 shows common adverse reactions associated with the use of RAYALDEE in the pooled placebo-controlled trials. These adverse reactions were not present at baseline, occurred more commonly on RAYALDEE than on placebo, and occurred in at least 1.4% of patients treated with RAYALDEE.

Table 1. Common Adverse Reactions in Placebo-controlled Trials Reported in ≥1.4% of RAYALDEE-Treated Subjects
Adverse Reaction | Placebo N=144 | RAYALDEE N=285
 | % | %
Anemia | 3.5 | 4.9
Nasopharyngitis | 2.8 | 4.9
Blood creatinine increased | 1.4 | 4.9
Dyspnea | 2.8 | 4.2
Cough | 2.1 | 3.5
Cardiac failure congestive | 0.7 | 3.5
Constipation | 2.8 | 3.2
Bronchitis | 0.7 | 2.8
Hyperkalemia | 0.7 | 2.5
Osteoarthritis | 0.7 | 2.1
Hyperuricemia | 0.7 | 1.8
Contusion | 0.0 | 1.8
Pneumonia | 0.7 | 1.4
Chronic obstructive pulmonary disease | 0.0 | 1.4

Increase in Serum Calcium

Patients randomized to RAYALDEE experienced a greater mean (SE) increase in serum calcium (P<0.001) than patients randomized to placebo [i.e., 0.2 (0.02) mg/dL on RAYALDEE versus 0.1 (0.03) mg/dL on placebo from baseline to trial end]. Six subjects (2%) in the RAYALDEE treatment group and no subjects (0%) in the placebo group required dose reductions for protocol-defined hypercalcemia (two consecutive serum calcium values greater than 10.3 mg/dL). A total of 4.2% of RAYALDEE treated subjects and 2.1% of placebo treated subjects experienced at least one elevation in serum calcium above the upper limit of normal (10.5 mg/dL).

Increase in Serum Phosphorus

Patients randomized to RAYALDEE experienced a greater mean (SE) increase in serum phosphorus than patients randomized to placebo [i.e., 0.2 (0.03) mg/dL on RAYALDEE versus 0.1 (0.04) mg/dL on placebo from baseline to trial end]. One subject (0.4%) in the RAYALDEE treatment group met protocol-defined hyperphosphatemia (two consecutive serum phosphorus values greater than 5.5 mg/dL deemed to be study drug related) compared to no subjects in the placebo group. A total of 45% of RAYALDEE treated subjects and 44% of placebo treated subjects experienced at least one elevation in serum phosphorus above the upper limit of normal (4.5 mg/dL).

7 DRUG INTERACTIONS

7.1 CYP3A Inhibitors

Cytochrome P450 inhibitors, such as ketoconazole, atazanavir, clarithromycin, indinavir, itraconazole, nefazodone, nelfinavir, ritonavir, saquinavir, telithromycin or voriconazole, may inhibit enzymes involved in vitamin D metabolism (CYP24A1 and CYP27B1), and may alter serum levels of calcifediol. Dose adjustment of RAYALDEE may be required, and serum 25-hydroxyvitamin D, intact PTH and serum calcium concentrations should be closely monitored if a patient initiates or discontinues therapy with a strong CYP3A4 inhibitor.

7.2 Thiazides

Thiazides are known to induce hypercalcemia by reducing excretion of calcium in the urine.

Concomitant administration of thiazides with RAYALDEE may cause hypercalcemia. Patients may require more frequent serum calcium monitoring in this setting [see Warnings and Precautions (5.1)].

7.3 Cholestyramine

Cholestyramine has been reported to reduce intestinal absorption of fat-soluble vitamins and may impair the absorption of calcifediol, the active ingredient in RAYALDEE. Dose adjustment of RAYALDEE may be required, and serum total 25-hydroxyvitamin D, intact PTH and serum calcium concentrations should be closely monitored if a patient initiates or discontinues therapy with cholestyramine.

7.4 Other Agents

Phenobarbital or other anticonvulsants or other compounds that stimulate microsomal hydroxylation reduce the half-life of calcifediol, the active ingredient in RAYALDEE. Dose adjustment of RAYALDEE may be required, and serum total 25-hydroxyvitamin D, intact PTH and serum calcium concentrations should be closely monitored if a patient initiates or discontinues therapy with phenobarbital or other anticonvulsants.

8 USE IN SPECIFIC POPULATIONS

8.1 Pregnancy

Risk Summary

There are no human data with calcifediol use in pregnant women to identify a drug-associated risk for major birth defects, miscarriage or adverse maternal or fetal outcomes. There are risks to the mother and fetus associated with chronic kidney disease in pregnancy (see Clinical Considerations). In animal reproduction studies, calcifediol increased skeletal and soft tissue malformation when rabbits were given once daily oral doses representing ≥8 times the human dose of 60 mcg/day, based on body surface area (mg/m^2), during the period of organogenesis. No adverse developmental effects were observed in rats given up to 10 times the human dose, based on body surface area (mg/m^2), during organogenesis.

The estimated background risk of major birth defects and miscarriage for the indicated population is unknown. In the U.S. general population, the estimated background risk of major birth defects and miscarriage in clinically recognized pregnancies is 2-4% and 15-20%, respectively.

Clinical Considerations

Disease-associated maternal and/or embryo/fetal risk

Chronic kidney disease in pregnancy increases the maternal risk for hypertension, miscarriage, preterm labor, and preeclampsia. Chronic kidney disease increases the fetal risk for intrauterine growth restriction (IUGR), prematurity, polyhydramnios, still birth, and low birth weight.

Data

Animal Data

Calcifediol was given orally to pregnant rats and rabbits during the period of organogenesis (in rats, from gestation day [GD] 6 to 15; in rabbits, from GD 6 to 18). Rats were given 0, 12, 40, 60 mcg/kg/day; and rabbits were given 0, 5, 25, 50 mcg/kg/day, representing up to 10 and 16 times, respectively, a human dose of 60 mcg/day, based on body surface area (mg/m^2).

In rats, no adverse developmental effects were observed at calcifediol doses up to 60 mcg/kg/day. In rabbits, increased incidences of domed skull, enlarged atrium of the heart, and dilatation of pulmonary artery, were observed at doses of 25 and 50 mcg/kg/day (representing 8 and 16 times the human dose of 60 mcg/day, respectively, based on body surface area (mg/m^2). Rats were given calcifediol during the pre/postnatal period (GD 15 to weaning). No adverse effects on gestation, parturition, lactation or survival of offspring were observed at calcifediol doses up to 60 mcg/kg/day.

8.2 Lactation

Risk Summary

There is no information available on the presence of calcifediol in human milk, the effects of the drug on the breastfed infant, or the effects of the drug on milk production. Infants potentially exposed to calcifediol through breast milk should be monitored for signs and symptoms of hypercalcemia (see Clinical Considerations). The developmental and health benefits of breastfeeding should be considered along with the mother’s clinical need for RAYALDEE and any potential adverse effects on the breastfed child from RAYALDEE or from the underlying maternal condition.

Clinical Considerations

Monitor infants exposed to calcifediol through breast milk for signs and symptoms of hypercalcemia, including seizures, vomiting, constipation and weight loss. Consider monitoring of serum calcium in the infant.

8.4 Pediatric Use

The safety and efficacy of RAYALDEE have not been established in pediatric patients.

8.5 Geriatric Use

Of the total number of subjects in phase 3 placebo-controlled clinical studies of RAYALDEE, 63% were ≥65 years of age and 22% were ≥75 years of age. No overall differences in the safety or efficacy of RAYALDEE were observed between subjects older than 65 years and younger subjects.

8.6 Renal Impairment

No difference in efficacy was observed between patients with stage 3 chronic kidney disease or those with stage 4 disease in subgroup analysis. Safety outcomes were similar in these subgroups. The safety and efficacy of RAYALDEE in the treatment of secondary hyperparathyroidism in patients with stage 2 or stage 5 chronic kidney disease and patients with end-stage renal disease on dialysis have not been established [see Indications and Usage (1)].

10 OVERDOSAGE

Excessive administration of RAYALDEE can cause hypercalciuria, hypercalcemia, hyperphosphatemia, or oversuppression of intact PTH. Common symptoms of vitamin D overdosage may include constipation, decreased appetite, dehydration, fatigue, irritability, muscle weakness, or vomiting.

Treatment of acute accidental overdosage with RAYALDEE should consist of general supportive measures. If the overdosage is discovered within a short time, induce emesis or perform gastric lavage to prevent further absorption. Obtain serial serum and urine calcium measurements, and assess any electrocardiographic abnormalities due to hypercalcemia. Discontinue supplemental calcium. Treat with standard medical care if persistent and markedly elevated serum calcium levels occur.

Calcifediol is not significantly removed by dialysis.

11 DESCRIPTION

Calcifediol, USP, the active ingredient in RAYALDEE, is synthetically manufactured as calcifediol monohydrate. Calcifediol is also known as calcidiol, 25-hydroxycholecalciferol or 25-hydroxyvitamin D3.

Calcifediol monohydrate is a white crystalline powder, has a calculated molecular weight of 418.65 and is soluble in alcohol and fatty oils but practically insoluble in water. Chemically, calcifediol monohydrate is (3β,5Z,7E)-9,10-secocholesta-5,7,10(19)-triene-3,25-diol monohydrate and its structural formula is:

RAYALDEE is formulated as extended-release capsules containing 30 mcg of calcifediol.

RAYALDEE is available as soft capsules or two-piece banded hard capsules containing 30 mcg of calcifediol for oral administration. Each capsule contains the following excipients: butylated hydroxytoluene, dehydrated alcohol, hypromellose, lauroyl polyoxylglycerides, mineral oil, monoglycerides and diglycerides, and paraffin. The soft capsule shells contain carrageenan, FD&C Blue #1, modified starch, purified water, sodium phosphate dibasic, sorbitol sorbitan solution, and titanium dioxide. Medium chain triglyceride (fractionated coconut) oil is used as a lubricant during manufacture, and trace amounts may be present in the final formulation. The hard capsule shells contain gellan gum, hypromellose, and titanium dioxide.

12 CLINICAL PHARMACOLOGY

12.1 Mechanism of Action

Calcifediol (25-hydroxyvitamin D3) is a prohormone of the active form of vitamin D3, calcitriol (1,25‑dihydroxyvitamin D3). Calcifediol is converted to calcitriol by cytochrome P450 27B1 (CYP27B1), also called 1-alpha hydroxylase, primarily in the kidney. Calcitriol binds to the vitamin D receptor in target tissues and activates vitamin D responsive pathways that result in increased intestinal absorption of calcium and phosphorus and reduced parathyroid hormone synthesis.

12.2 Pharmacodynamics

In repeat-dose clinical studies with RAYALDEE, increased levels of serum total 25-hydroxyvitamin D were associated with corresponding increases in serum total 1,25‑dihydroxyvitamin D concentrations and reductions in circulating plasma intact PTH observed within the first two weeks of RAYALDEE treatment [see Clinical Studies (14)].

12.3 Pharmacokinetics

Absorption

Exposure to calcifediol increased proportionally over the dose range of 30 to 90 mcg following repeated daily administration of RAYALDEE at bedtime to subjects with secondary hyperparathyroidism, chronic kidney disease and vitamin D insufficiency. Steady-state levels of serum total 25-hydroxyvitamin D were reached after approximately 3 months [see Clinical Studies (14)].

Effect of Food

Food effect studies with a supratherapeutic dose of RAYALDEE at 450 mcg or 900 mcg in healthy subjects resulted in an approximately 5-fold increase in maximum serum calcifediol concentration (Cmax) and a 3.5-fold increase in AUC0-t when administered with a high fat, high calorie meal compared to fasting.

Distribution

Calcifediol is extensively bound to plasma proteins (>98%). The mean apparent volume of distribution is 8.8 L in healthy subjects following a single oral dose of RAYALDEE, and 30.1 L in subjects with stage 3 or 4 chronic kidney disease following repeated dosing.

Elimination

The mean elimination half-life of calcifediol is approximately 11 days in healthy individuals following a single dose of RAYALDEE, and approximately 25 days in patients with stage 3 or stage 4 chronic kidney disease following repeated once daily dosing.

Metabolism

Production of calcitriol from calcifediol is catalyzed by the 1-alpha-hydroxylase enzyme, CYP27B1, located in the kidney and other tissues. CYP24A1, located in all vitamin D-responsive tissues, catabolizes both calcifediol and calcitriol to inactive metabolites.

Excretion

Excretion of calcifediol occurs primarily through the biliary fecal route.

Specific Populations

Age, gender and race had no meaningful impact on steady-state concentrations of calcifediol following RAYALDEE administration.

Patients with Renal Impairment

There was no meaningful difference in calcifediol steady-state concentrations following repeated RAYALDEE administration in patients with stage 3 or stage 4 chronic kidney disease.

Patients with Hepatic Impairment

The pharmacokinetics of calcifediol have not been investigated in patients with hepatic impairment.

13 NONCLINICAL TOXICOLOGY

13.1 Carcinogenesis, Mutagenesis, Impairment of Fertility

No neoplastic changes attributable to calcifediol were observed at subcutaneous doses of 3, 10 and 33 mcg/kg/day in a 26-week rasH2 transgenic mouse study.

In vitro or in vivo mutagenicity studies have not been performed with RAYALDEE.

Calcifediol has not been shown to have significant effects on fertility in rats.

14 CLINICAL STUDIES

The efficacy and safety of RAYALDEE were evaluated in two identical multicenter, randomized, placebo-controlled, double-blind trials in patients with secondary hyperparathyroidism, stage 3 or 4 chronic kidney disease and serum total 25-hydroxyvitamin D levels between 10 and 30 ng/mL. Subjects were stratified by chronic kidney disease stage and randomized in a 2:1 ratio to receive RAYALDEE or a matching placebo at bedtime over 26 weeks. The dose of RAYALDEE was 30 mcg once daily for the first 12 weeks and either 30 or 60 mcg once daily for the last 14 weeks. The dose was increased to 60 mcg at the start of week 13 if the plasma intact PTH level was greater than 70 pg/mL, the serum 25-hydroxyvitamin D level was less than 65 ng/mL and the serum calcium level was less than 9.8 mg/dL.

A total of 213 subjects were randomized in one trial (72 received placebo and 141 received RAYALDEE), and 216 subjects were randomized in the second trial (72 received placebo and 144 received RAYALDEE). The subjects’ mean age was 66 years (range 25-85), 50% were male, 65% White, 32% African-American or Black and 3% Other. At baseline, subjects had secondary hyperparathyroidism, and stage 3 (52%) or stage 4 (48%) chronic kidney disease without macroalbuminuria. The most common causes of chronic kidney disease were diabetes and hypertension and the mean estimated GFR was 31 mL/min/1.73m^2. Mean baseline intact PTH was 130 pg/mL for subjects with stage 3 disease (n=222) and 166 pg/mL for subjects with stage 4 disease (n=207). Mean serum calcium was 9.2 mg/dL, mean serum phosphorus was 3.7 mg/dL and mean serum 25-hydroxyvitamin D was 20 ng/mL. Of the 429 subjects randomized, 354 (83%) completed the studies.

The primary analysis compared the proportion of individuals who experienced an at least 30% reduction in plasma intact PTH from baseline to end of trial (average of weeks 20, 22, 24 and 26). A larger proportion of patients randomized to RAYALDEE experienced an at least 30% reduction in plasma intact PTH from baseline compared to placebo in both trials [33% versus 8% in the first trial (P<0.001) and 34% versus 7% in the second trial (P<0.001)].

A description of mean (SE) percent change in plasma intact PTH from baseline across study visits in the two trials combined is shown in Figure 1. Serum total 25-hydroxyvitamin D levels increased to at least 30 ng/mL in 80% and 83% of subjects treated with RAYALDEE vs. 3% and 7% of subjects treated with placebo (P<0.001) in the two studies, respectively. Average steady-state 25-hydroxyvitamin D levels were 50 and 56 ng/mL for subjects receiving 30 mcg daily, and 69 and 67 ng/mL for subjects receiving 60 mcg daily, in the first and second studies, respectively.

Figure 1. Mean (±SE) Percent Change from Baseline in Plasma Intact PTH in the Per Protocol Populations (Pooled Data from Two Phase 3 Studies)

The Per Protocol (PP) population consisted of all subjects with at least 2 intact PTH values in the calculated baseline and efficacy assessment period (EAP) values and who did not have a major protocol deviation during the treatment period of the study. The PP population comprised 83% of randomized subjects.

16 HOW SUPPLIED/STORAGE AND HANDLING

RAYALDEE is supplied as 30 mcg calcifediol in blue, oval extended-release soft capsules, imprinted O:

Bottles of 30 [NDC 70301-1001-1]

Bottles of 60 [NDC 70301-1001-2]

RAYALDEE is also supplied as 30 mcg calcifediol in white extended-release two-piece banded hard capsules, imprinted O on the cap and 30 on the body:

Bottles of 30 [NDC 70301-1002-1]

Bottles of 60 [NDC 70301-1002-2]

Store at 20 to 25°C (68 to 77°F); excursions permitted to 15 to 30°C (59 to 86°F) [see USP Controlled Room Temperature].

17 PATIENT COUNSELING INFORMATION

- Inform patients to take RAYALDEE at bedtime and to swallow the capsules whole.
- Inform patients if they miss a dose, to take RAYALDEE at the next scheduled time. Do not take an extra dose to make up for the missed dose.
- Inform patients that they will need routine monitoring of laboratory parameters such as calcium, iPTH and total 25-hydroxyvitamin D while taking RAYALDEE.
- Advise patients to contact a health care provider if they develop symptoms of elevated calcium (e.g., feeling tired, having difficulty thinking clearly, loss of appetite, nausea, vomiting, constipation, increased thirst, increased urination or weight loss).
- Advise patients to inform their physician of all use of medications, including prescription and nonprescription drugs, supplements and herbal preparations, and of any changes in medical condition. Patients should also be advised to inform their physicians, when receiving a newly prescribed medication, that they are taking RAYALDEE.
- Inform lactating women about the need to monitor infants exposed to RAYALDEE through breast milk for signs of hypercalcemia to include seizures, vomiting, constipation and weight loss [see Use in Specific Populations (8.2)].

RAYALDEE® is a registered trademark of Eirgen Pharma Ltd.

Patent: https://www.opko.com/what-we-do/our-research/patents

Manufactured for:
OPKO Pharmaceuticals, LLC
4400 Biscayne Blvd.
Miami FL 33137 USA

© 2024 OPKO Pharmaceuticals, LLC. All rights reserved.

PRINCIPAL DISPLAY PANEL NDC: 70301-1001-1 - 30-count Bottle Label

30-count Soft Capsule Bottle Label

NDC 70301-1001-1 OPKO

Rayaldee® (calcifediol)
Extended-Release Capsules

30 mcg

Rx only

Each capsule contains:
30 mcg calcifediol
See package insert for full
prescribing information
30 Capsules

Manufactured for:
OPKO Pharmaceuticals, LLC
4400 Biscayne Blvd
Miami FL 33137

Rev. 03/21

PC2192

Store between 20 - 25°C
(68-77°F) excursions
permitted to 15 - 30°C
(59 - 86°F) see [USP
controlled room temperature]

PRINCIPAL DISPLAY PANEL NDC: 70301-1002-1 - 30-count Bottle Label

30-count Hard Capsule Bottle Label

NDC 70301-1002-1 OPKO
Rx only

Rayaldee®
calcifediol ER capsules
30 mcg

Each capsule contains:
30 mcg calcifediol
See package insert for full
prescribing information
30 Capsules

Manufactured for:
OPKO Pharmaceuticals, LLC
4400 Biscayne Blvd
Miami FL 33137

Rev. 06/24

PC2569

Store between 20 - 25°C
(68-77°F) excursions
permitted to 15 - 30°C
(59 - 86°F) see [USP
controlled room temperature]